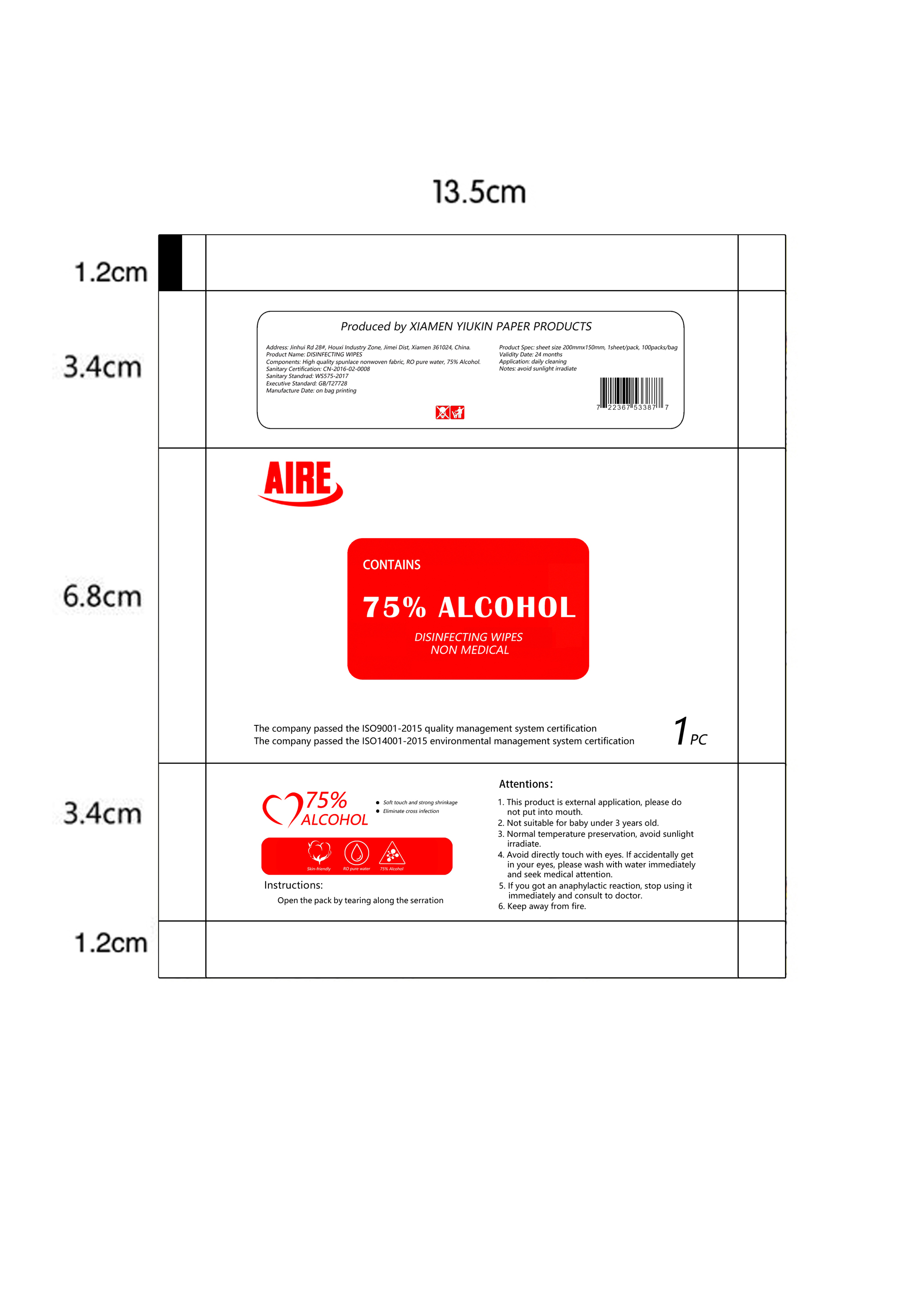 DRUG LABEL: Disinfecting Wipes
NDC: 79288-006 | Form: CLOTH
Manufacturer: Xiamen Yiukin Paper Products Co.,ltd
Category: otc | Type: HUMAN OTC DRUG LABEL
Date: 20200722

ACTIVE INGREDIENTS: ALCOHOL 8 mL/100 g; BENZALKONIUM CHLORIDE 0.08 g/100 g
INACTIVE INGREDIENTS: PROPYLENE GLYCOL; CETYLPYRIDINIUM CHLORIDE; WATER

Disinfecting Wipes

Active Ingredient(s)

Alcohol 8%. Purpose: Antiseptic

benzalkonium chloride 0.08%. Purpose: Antiseptic

Purpose

Antiseptic

Use

Daily cleaning

Warnings

1. This product is for external use, please do not put into mouth.
2. Not suitable for baby under 3 years old.
3. Normal temperture perservation, avoid sunlight irradiate.
4. Avoid directly touch with eyes. If accidentally get in your eyes, please wash with water immediately and seek medical attention.
5. If you got an anaphylactic reaction, stop using it immediately and consult to doctor.
6. Keep away from fire.

Not suitable for baby under 3 years old.

WHEN USING

Avoid directly touch with eyes. If accidentally get in your eyes, please wash with water immediately and seek medical attention.
If you got an anaphylactic reaction, stop using it immediately and consult to doctor.

STOP USE

If you got an anaphylactic reaction, stop using it immediately and consult to doctor.

KEEP OUT OF REACH OF CHILDREN

This product is for external use, please do not put into mouth.
Not suitable for baby under 3 years old.

Directions

Open the pack by tearing along the serration

Other information

avoid sunlight irradiate.

Inactive ingredients

water, Propylene glycol, Cetylpyridinium chloride

Package Label - Principal Display Panel

1 PC NDC: 79288-006-01